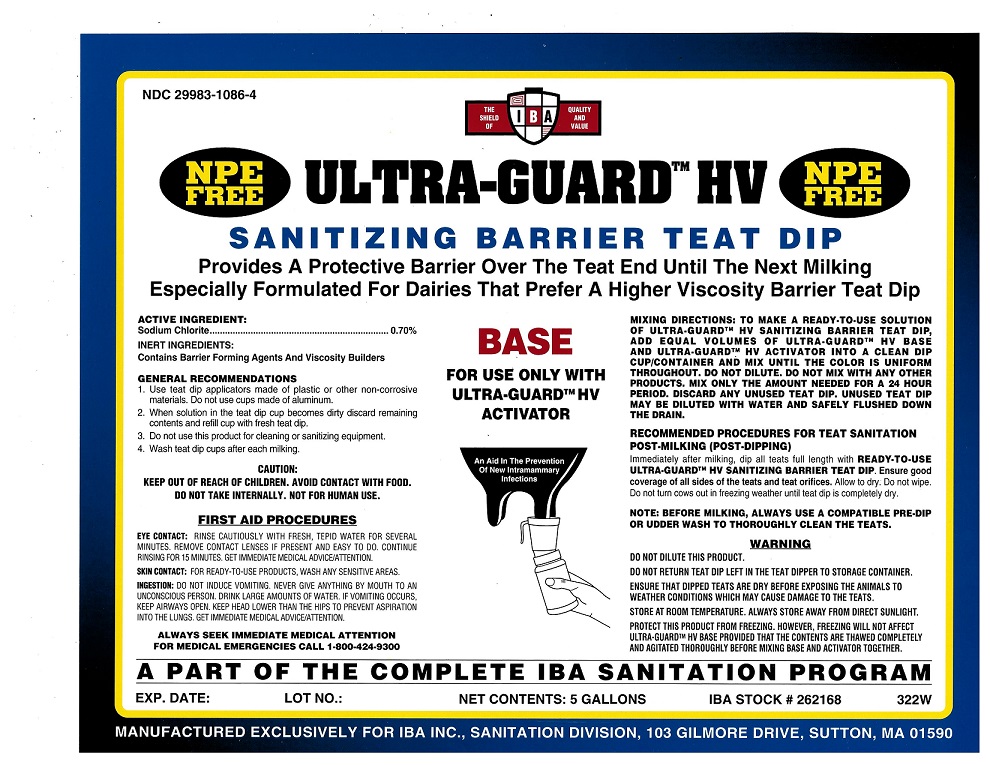 DRUG LABEL: Ultra-Guard HV Base
NDC: 29983-1086 | Form: LIQUID
Manufacturer: IBA
Category: animal | Type: OTC ANIMAL DRUG LABEL
Date: 20251211

ACTIVE INGREDIENTS: SODIUM CHLORITE 0.70 kg/100 kg

Ultra-Guard HV Base

Active Ingredient

Sodium Chlorite 0.7%

Inert Ingredients

Contains barrier forming agents and viscosity builders

Mixing Directions

To make a ready-to-use solution of Ultra-Guard HV Saitizing Barrier Teat Dip, add equal volumes of Ultra-Guard HV Base and Ultra-Guard HV Activator into a clean dip cup/container and mix until the color is uniform throughout. Do not dilute. Do not mix with any other products. Mix only the amount needed for a 24 hour period. Discard any unused teat dip. Unused teat dip may be diluted with water and safely flushed down the drain.

Recommended Procedures for Teat Sanitation

POST-MILKING (POST-DIPPING)
Immediately after milking, dip all teats full length with READY-TO-USE OPTI-GUARD TEAT DIP. Ensure good coverage of all sides of the teats and teat orifices. Allow to dry. Do not wipe. Do not turn cows out in freezing weather until teat dip is completely dry.

Note: Before milking, always use a compatible pre-dip or udder wash to thoroughly clean the teats.

First Aid

EYE CONTACT: Rinse cautiously with fresh, tepid water for several minutes. Remove contact lenses if present and easy to do. Continue rinsing for 15 minutes. Get immediate medical advice/attention. SKIN CONTACT: For RTU products wash any sensitive areas. INGESTION: Do not induce vomiting. Never give anything by mouth to an unconscious person. Drink large amounts of water. If vomiting occurs, keep airways open. Keep head lower than the hips to prevent aspiration into the lungs. Get immediate medical advice/attention.

Caution

Keep out of reach of children. Avoid contact with food. Do not take internally. Not for human use.

Warning

Do not dilute this product.

Do not return teat dip left in the teat dipper to storage container.

Ensure that dipped teats are dry before exposing the animals to weather conditions which may cause damage to the teats.

Store at room temperature. Always store away from direct sunlight.

Protect this product from freezing. However, freezing will not affect Ultra-Guard HV Base provided that the contents are thawed completely and agitated thoroughly before mixing base and activator together.